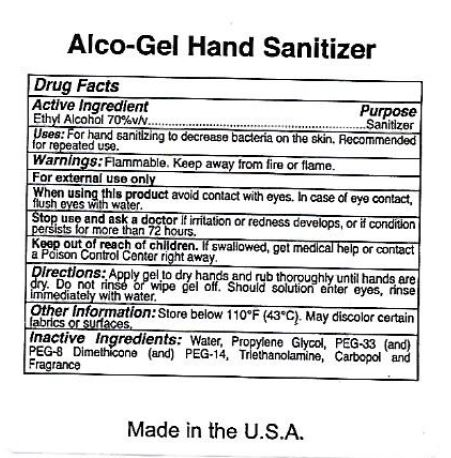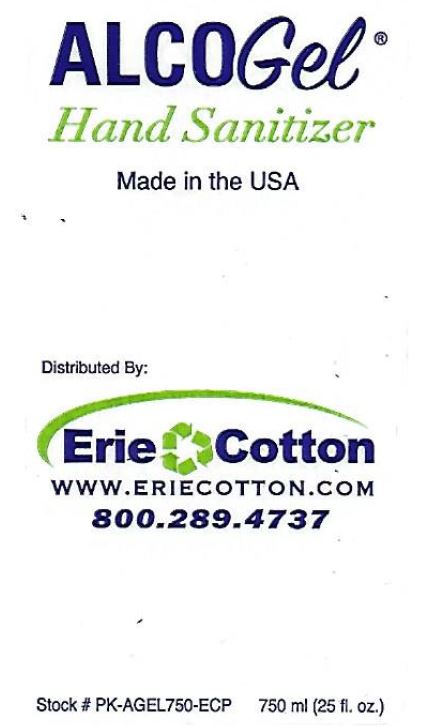 DRUG LABEL: ALCOGel Hand Sanitizer
NDC: 82825-001 | Form: GEL
Manufacturer: Erie Cotton Products Inc.
Category: otc | Type: HUMAN OTC DRUG LABEL
Date: 20241125

ACTIVE INGREDIENTS: ALCOHOL 70 mL/100 mL
INACTIVE INGREDIENTS: PROPYLENE GLYCOL; TROLAMINE; WATER; POLYETHYLENE GLYCOL 1500; POLYETHYLENE GLYCOL 400; POLYETHYLENE GLYCOL 700

82825-001

Active ingredient

Ethyl Alcohol 70%v/v

Purpose

Sanitizer

Uses:

For hand sanitizng to decrease bacteria on the skin.

Recommended for repeated use.

Warnings:Flammable. Keep away from fire or flame.

For external use only

When using this productavoid contact with eyes.

In case of eye contact, flush eyes with water.

Stop use and ask a doctorif irritation or redness develops, or if condition persists for more than 72 hours.

Keep out of reach of children.

If swallowed, get medical help or contact a Poison Control Center right away.

Directions:

Apply gel to dry hands and rub thoroughly until hands are dry.

Do not rinse or wipe gel off.

Should solution enter eyes, rinse immediately with water.

Other Information:

Store below 110 F (43 C).

May discolor certain fabrics or surfaces.

Inactive ingredients:

Water, Propylene Glycol, PEG-33 (and) PEG-8 Dimethicone (and) PEG-14, Triethanolamine, Carbopol and Fragrance

PACKAGE LABEL

ALCOGeL

Hand Sanitizer

Made in the USA

Distributed By:

Erie Cotton

www.ErieCotton.com

800.289.4737

Stock # PK-AGEL750-ECP 750ml (25 fl.oz.)